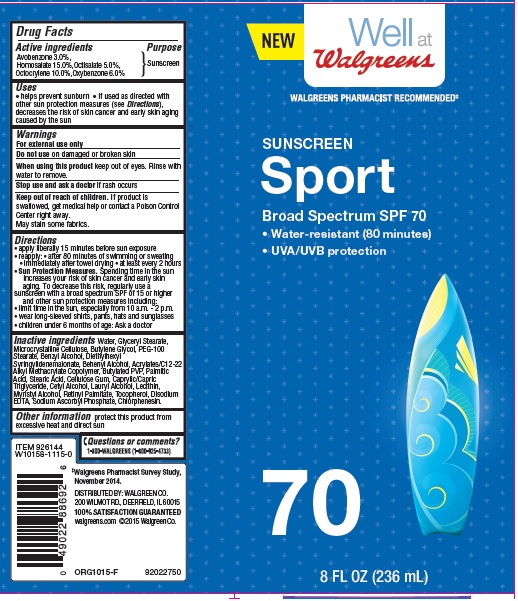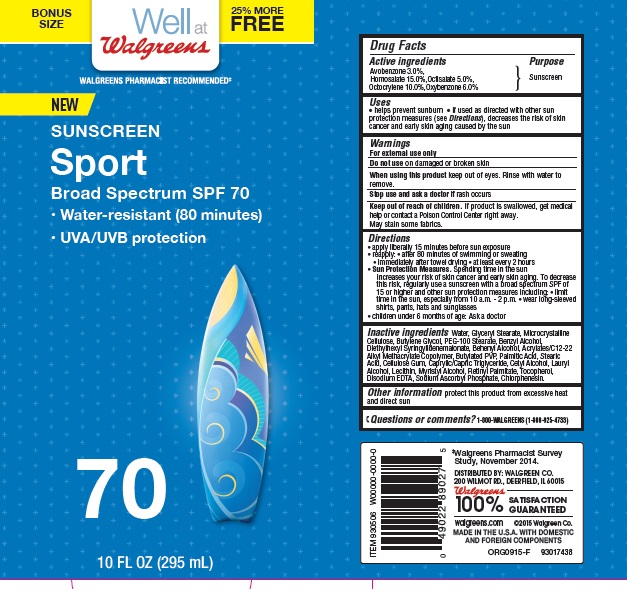 DRUG LABEL: Walgreens Sunscreen Sport SFP 70
NDC: 0363-1671 | Form: LOTION
Manufacturer: Walgreens Co.
Category: otc | Type: HUMAN OTC DRUG LABEL
Date: 20160309

ACTIVE INGREDIENTS: AVOBENZONE 3 g/100 g; HOMOSALATE  15 g/100 g; OCTISALATE 5 g/100 g; OCTOCRYLENE 10 g/100 g; OXYBENZONE 6 g/100 g
INACTIVE INGREDIENTS: WATER; GLYCERYL MONOSTEARATE; CELLULOSE, MICROCRYSTALLINE; BUTYLENE GLYCOL; PEG-100 STEARATE; BENZYL ALCOHOL; DIETHYLHEXYL SYRINGYLIDENEMALONATE; DOCOSANOL; PALMITIC ACID; STEARIC ACID; CARBOXYMETHYLCELLULOSE SODIUM, UNSPECIFIED FORM; MEDIUM-CHAIN TRIGLYCERIDES; CETYL ALCOHOL; LAURYL ALCOHOL; MYRISTYL ALCOHOL; VITAMIN A PALMITATE; EDETATE DISODIUM; SODIUM ASCORBYL PHOSPHATE; CHLORPHENESIN

Drug Facts

Active ingredients

Avobenzone 3.0%,Homosalate 15.0%, Octisalate 5.0%, Octocrylene 10.0%, Oxybenzone 6.0%

Purpose

Sunscreen

Uses

• helps prevent sunburn

• if used as directed with other sun protection measures (see Directions), decreases the risk of skin cancer and early skin aging caused by the sun

Warnings

For external use only

Do not use

on damaged or broken skin

When using this product

keep out of eyes. Rinse with water to remove.

Stop use and ask a doctor

if rash occurs

Keep out of reach of children.

If product is swallowed, get medical help or contact a Poison Control Center right away.

• May stain some fabrics

Directions

• apply liberally 15 minutes before sun exposure

• reapply:

• after 80 minutes of swimming or sweating

• immediately after towel drying

• at least every 2 hours

Sun Protection Measures: Spending time in the sun increases your risk of skin cancer and early skin

aging. To decrease this risk, regularly use a sunscreen with a broad spectrum SPF of 15 or higher and other protection measures including:

• limit time in the sun, especially from 10 a.m. to 2 p.m.

• wear long-sleeved shirts, pants, hats, and sunglasses

• children under 6 months: Ask a doctor

Inactive ingredients

Water, Glyceryl Stearate, Microcrystalline Cellulose, Butylene Glycol, PEG-100 Stearate, Benzyl Alcohol, Diethylhexyl Syringylidenemalonate, Behenyl Alcohol, Acrylates/C12-22 Alkyl ethacrylate Copolymer, Butylated PVP, Palmitic Acid, Stearic Acid, Cellulose Gum, Caprylic/Capric Triglyceride, Cetyl Alcohol, Lauryl Alcohol, Lecithin, Myristyl Alcohol, Retinyl Palmitate, ocopherol, Disodium EDTA, Sodium Ascorbyl Phosphate, Chlorphenesin.

Other information

• protect this product from excessive heat and direct sun

Questions or comments?

1-800-WALGREENS (1-800-925-4133)

Principle Display Label

NDC: 0363-1671-26

NEW

Well at Walgreens

WALGREENS PHARMACIST RECOMMENDED*

SUNSCREEN

Sport

Broad Spectrum SPF 70

- Water-resistant (80 minutes)

- UVA/UVB Protection

70

8 FL OZ (236 mL)

NDC: 0363-1671-27

BONUS SIZE

Well at Walgreens

20% MORE FREE

WALGREENS PHARMACIST RECOMMENDED*

NEW

SUNSCREEN

Sport

Broad Spectrum SPF 70

- Water Resistant (80 minutes)

- UVA/UVB Protection

70

10 FL OZ (295 mL)